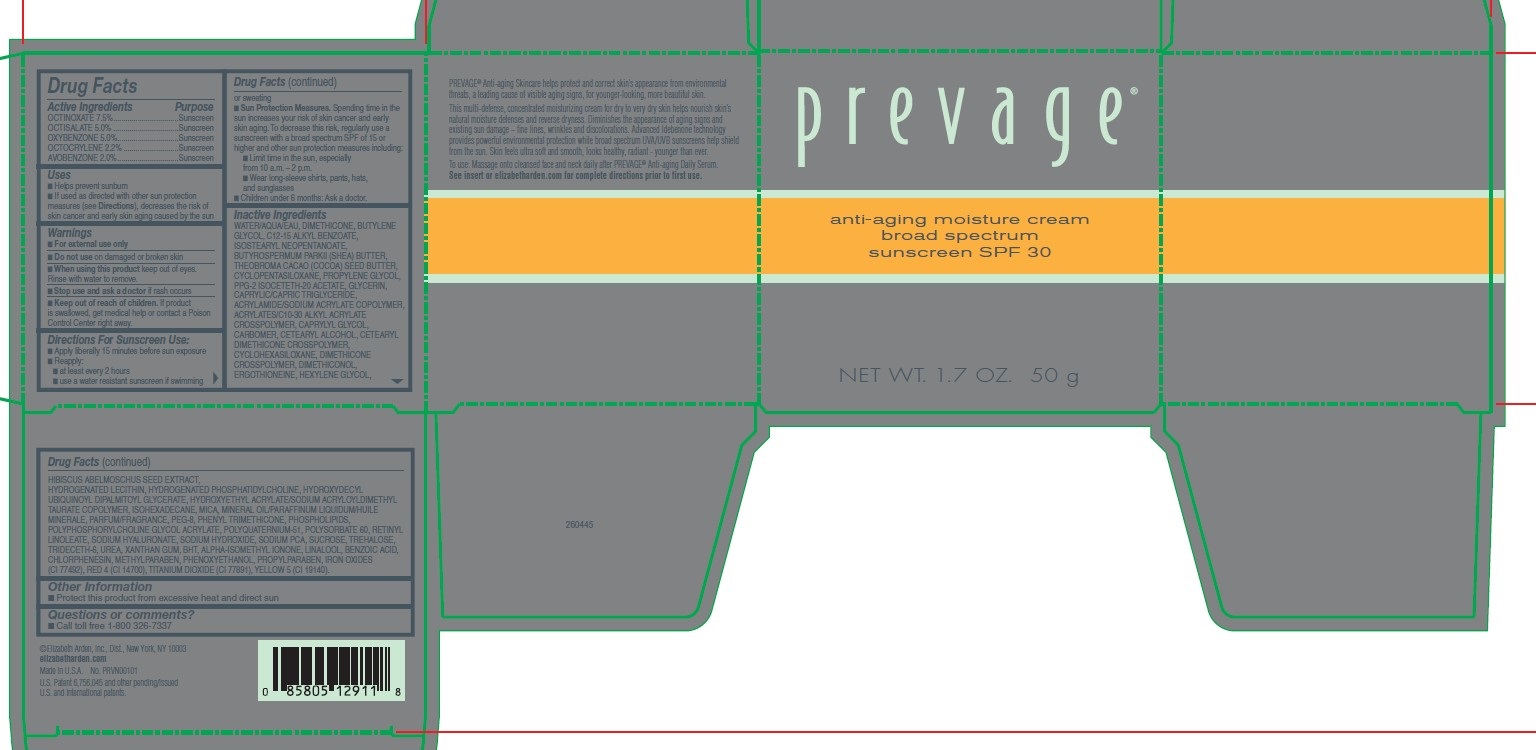 DRUG LABEL: Prevage Anti-aging Moisture Cream
NDC: 10967-688 | Form: CREAM
Manufacturer: Revlon Consumer Products Corp
Category: otc | Type: HUMAN OTC DRUG LABEL
Date: 20251229

ACTIVE INGREDIENTS: AVOBENZONE 2 mg/1 g; OCTINOXATE 7.5 mg/1 g; OXYBENZONE 5 mg/1 g; OCTOCRYLENE 2.2 mg/1 g; OCTISALATE 5 mg/1 g
INACTIVE INGREDIENTS: HYDROXYDECYL UBIQUINOYL DIPALMITOYL GLYCERATE; BUTYLATED HYDROXYTOLUENE; TITANIUM DIOXIDE; WATER; PROPYLENE GLYCOL; HYDROGENATED SOYBEAN LECITHIN; ISOHEXADECANE; MICA; SHEA BUTTER; SODIUM PYRROLIDONE CARBOXYLATE; CHLORPHENESIN; METHYLPARABEN; PROPYLPARABEN; CAPRYLYL GLYCOL; CARBOMER 1342; BUTYLENE GLYCOL; HEXYLENE GLYCOL; DIMETHICONE 1000; ISOSTEARYL NEOPENTANOATE; PPG-2 ISOCETETH-20 ACETATE; CYCLOMETHICONE 6; DIMETHICONE CROSSPOLYMER (450000 MPA.S AT 12% IN CYCLOPENTASILOXANE); DIMETHICONOL (100000 CST); PHENYL TRIMETHICONE; EGG PHOSPHOLIPIDS; TRIDECETH-6; COCOA BUTTER; CARBOMER INTERPOLYMER TYPE A (55000 CPS); CETOSTEARYL ALCOHOL; GLYCERIN; POLYQUATERNIUM-51 (2-METHACRYLOYLOXYETHYL PHOSPHORYLCHOLINE/N-BUTYL METHACRYLATE; 3:7); PEG-9 DIGLYCIDYL ETHER/SODIUM HYALURONATE CROSSPOLYMER; TREHALOSE; SODIUM HYDROXIDE; LINALOOL, (+/-)-; FERRIC OXIDE RED; ACRYLAMIDE; CYCLOMETHICONE 5; ERGOTHIONEINE; XANTHAN GUM; ISOMETHYL-.ALPHA.-IONONE; BENZOIC ACID; PHENOXYETHANOL; UREA; HYDROXYETHYL ACRYLATE/SODIUM ACRYLOYLDIMETHYL TAURATE COPOLYMER (45000 MPA.S AT 1%); CETYL DIMETHICONE 150; MEDIUM-CHAIN TRIGLYCERIDES; ALKYL (C12-15) BENZOATE; ABELMOSCHUS MOSCHATUS SEED; POLYSORBATE 60; RETINYL LINOLEATE; SUCROSE

Prevage Anti-Aging Moisture Cream SPF30

Inactive ingredients

WATER/AQUA/EAU, DIMETHICONE, BUTYLENE GLYCOL, C12-15 ALKYL BENZOATE, ISOSTEARYL NEOPENTANOATE, BUTYROSPERMUM PARKII (SHEA) BUTTER, THEOBROMA CACAO (COCOA) SEED BUTTER, CYCLOPENTASILOXANE, PROPYLENE GLYCOL, PPG-2 ISOCETETH-20 ACETATE, GLYCERIN, CAPRYLIC/CAPRIC TRIGLYCERIDE, ACRYLAMIDE/SODIUM ACRYLATE COPOLYMER, ACRYLATES/C10-30 ALKYL ACRYLATE CROSSPOLYMER, CAPRYLYL GLYCOL, CARBOMER, CETEARYL ALCOHOL, CETEARYL DIMETHICONE CROSSPOLYMER, CYCLOHEXASILOXANE, DIMETHICONE CROSSPOLYMER, DIMETHICONOL, ERGOTHIONEINE, HEXYLENE GLYCOL, HIBISCUS ABELMOSCHUS SEED EXTRACT, HYDROGENATED LECITHIN, HYDROGENATED PHOSPHATIDYLCHOLINE, HYDROXYDECYL UBIQUINOYL DIPALMITOYL GLYCERATE, HYDROXYETHYL ACRYLATE/SODIUM ACRYLOYLDIMETHYL TAURATE COPOLYMER, ISOHEXADECANE, MICA, MINERAL OIL/PARAFFINUM LIQUIDUM/HUILE MINERALE, PARFUM/FRAGRANCE, PEG-8, PHENYL TRIMETHICONE, PHOSPHOLIPIDS, POLYPHOSPHORYLCHOLINE GLYCOL ACRYLATE, POLYQUATERNIUM-51, POLYSORBATE 60, RETINYL LINOLEATE, SODIUM HYALURONATE, SODIUM HYDROXIDE, SODIUM PCA, SUCROSE, TREHALOSE, TRIDECETH-6, UREA, XANTHAN GUM, BHT, ALPHA-ISOMETHYL IONONE, LINALOOL, BENZOIC ACID, CHLORPHENESIN, METHYLPARABEN, PHENOXYETHANOL, PROPYLPARABEN, IRON OXIDES (CI 77492), RED 4 (CI 14700), TITANIUM DIOXIDE (CI 77891), YELLOW 5 (CI 19140)

Active Ingredient Section

OCTINOXATE 7.5%

OCTISALATE 5.0%

OXYBENZONE 5.0%

OCTOCRYLENE 2.2%

AVOBENZONE 2.0%

Warnings

For external use only. Do not use on damaged or broken skin. When using this product keep out of eyes. Rinse with water to remove. Stop use and ask a doctor if rash occurs.

When using this product keep out of eyes. Rinse with water to remove. Stop use and ask a doctor if rash occurs.

Keep out of reach of children. If product is swallowed, get medical help or contact a Poison Control Center right away.

DOSAGE AND ADMINISTRATION

Apply liberally 15 minutes before sun exposure
Reapply at least every 2 hours

INDICATIONS AND USAGE

- Helps prevent sunburn
- If used as directed with other sun protection measures (see Directions), decreases the risk of skin cancer and early skin againg caused by the sun

PURPOSE

Sunscreen